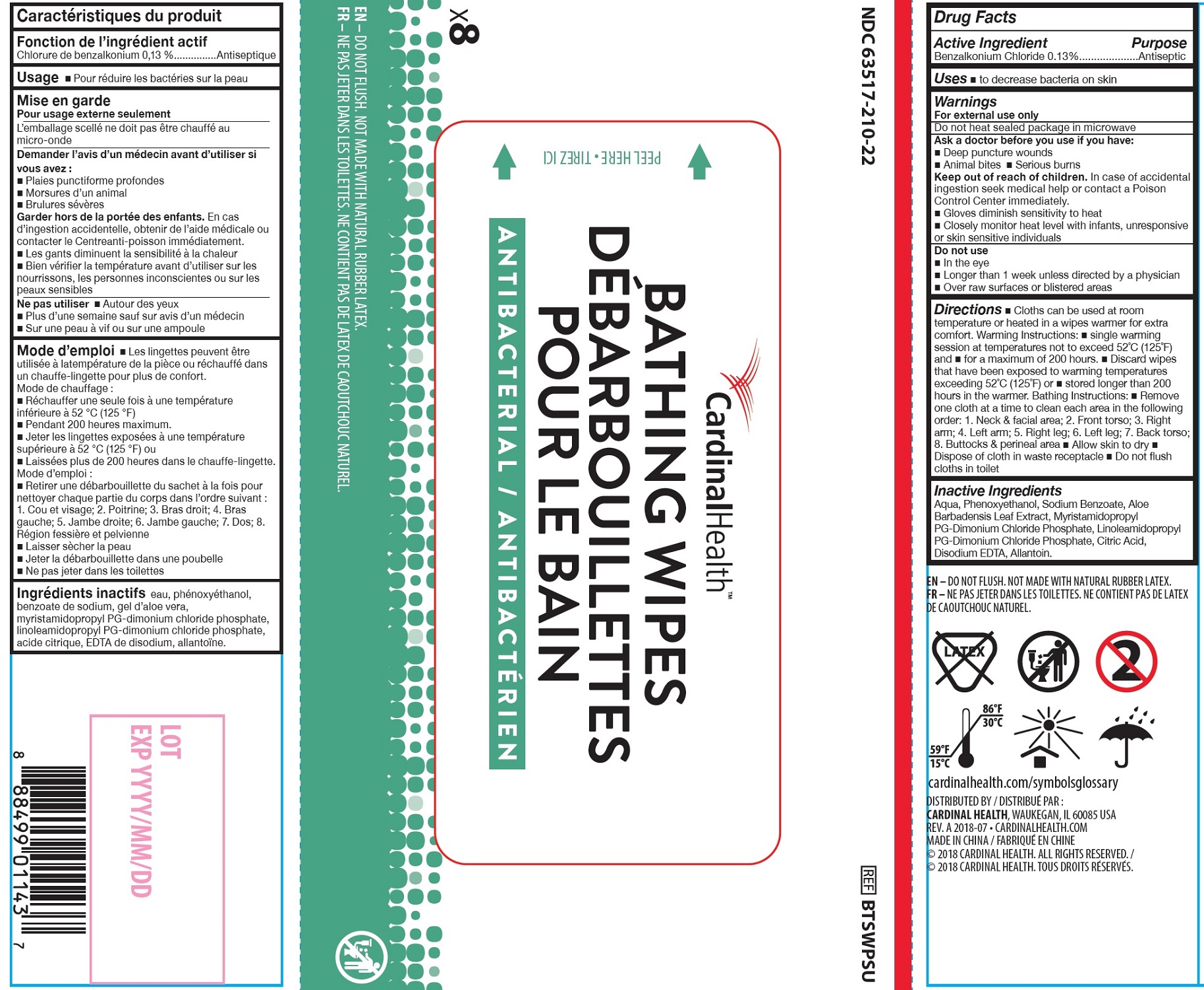 DRUG LABEL: Antibacterial Bathing
NDC: 63517-210 | Form: CLOTH
Manufacturer: Cardinal Health, Inc.
Category: otc | Type: HUMAN OTC DRUG LABEL
Date: 20250106

ACTIVE INGREDIENTS: BENZALKONIUM CHLORIDE 1.3 mg/1 mL
INACTIVE INGREDIENTS: PHENOXYETHANOL; SODIUM BENZOATE; ALOE VERA LEAF; MYRISTAMIDOPROPYL PROPYLENE GLYCOL-DIMONIUM CHLORIDE PHOSPHATE; LINOLEAMIDOPROPYL PROPYLENE GLYCOL-DIMONIUM CHLORIDE PHOSPHATE; CITRIC ACID MONOHYDRATE; EDETATE DISODIUM; ALLANTOIN; WATER

Antibacterial Bathing Wipe

Active Ingredient

Benzalkonium Chloride 0.13%

Purpose

Antiseptic

Uses

- to decrease bacteria on skin

Warnings

For external use only

Do not heat sealed package in microwave

Ask a doctor before you use if you have:

- Deep puncture wounds
- Animal bites
- Serious burns

Keep out of reach of children.

- In case of accidental ingestion seek medical help or contact a Poison Control Center immediately.
- Gloves diminish sensitivity to heat
- Closely monitor heat level with infants, unresponsive or skin sensitive individuals

Do not use

- In the eye
- Longer than 1 week unless directed by a physician
- Over raw surfaces or blistered areas

Directions

- Cloths can be used at room temperature or heated in a wipes warmer for extra comfort. Warming Instructions:
- single warming session at temperatures not to exceed 52˚C (125˚F) and
- for a maximum of 200 hours.
- Discard wipes that have been exposed to warming temperatures exceeding 52˚C (125˚F) or
- stored longer than 200 hours in the warmer. Bathing Instructions:
- Remove one cloth at a time to clean each area in the following order: 1. Neck & facial area; 2. Front torso; 3. Right arm; 4. Left arm; 5. Right leg; 6. Left leg; 7. Back torso; 8. Buttocks & perineal area
- Allow skin to dry
- Dispose of cloth in waste receptacle
- Do not flush cloths in toilet

Inactive Ingredients

Aqua, Phenoxyethanol, Sodium Benzoate, Aloe Barbadensis Leaf Extract, Myristamidopropyl PG-Dimonium Chloride Phosphate, Linoleamidopropyl PG-Dimonium Chloride Phosphate, Citric Acid, Disodium EDTA, Allantoin.